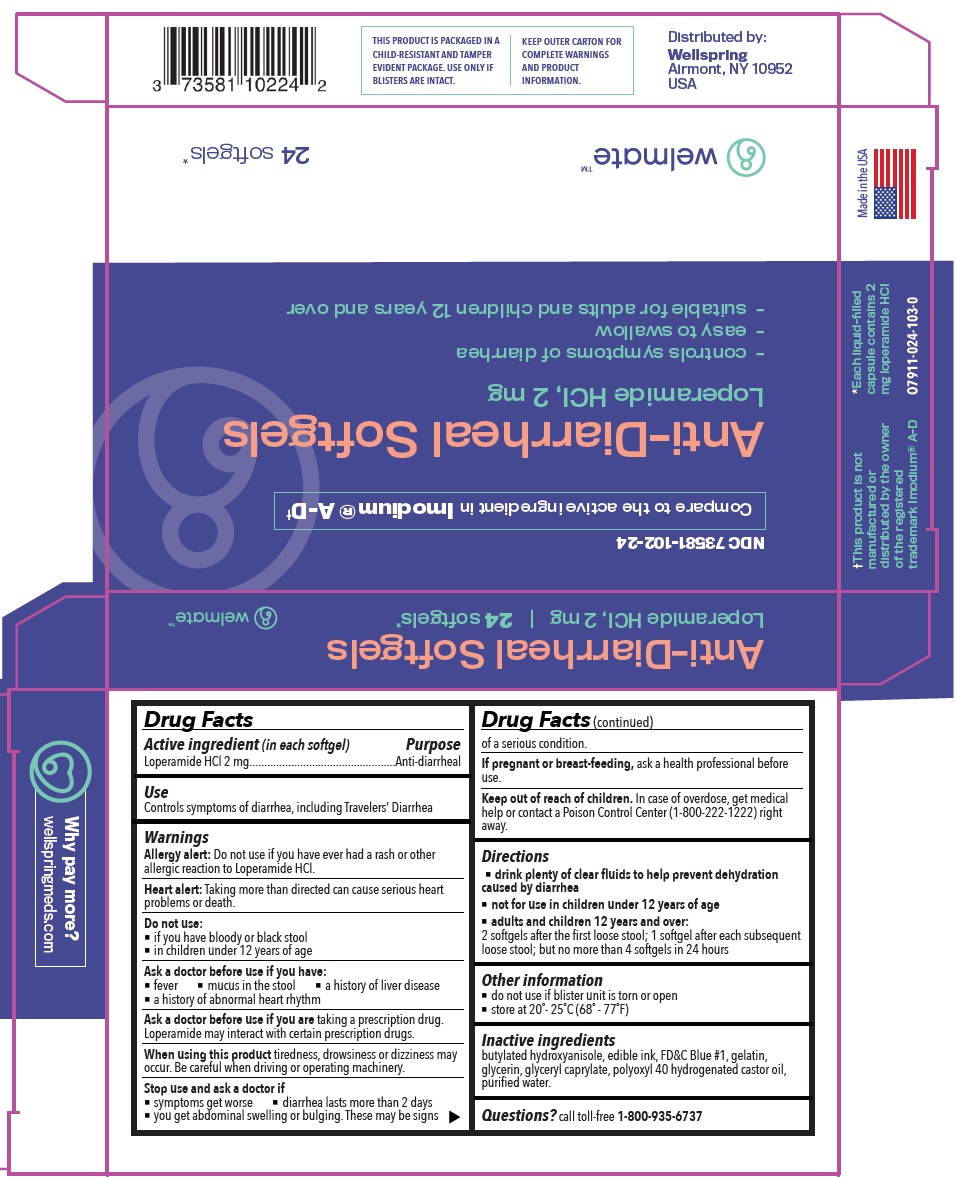 DRUG LABEL: WELMATE Anti Diarrheal Loperamide HCl Softgels
NDC: 73581-102 | Form: CAPSULE
Manufacturer: YYBA CORP
Category: otc | Type: HUMAN OTC DRUG LABEL
Date: 20221101

ACTIVE INGREDIENTS: LOPERAMIDE HYDROCHLORIDE 2 mg/1 1
INACTIVE INGREDIENTS: BUTYLATED HYDROXYANISOLE; FD&C BLUE NO. 1; GELATIN; GLYCERIN; GLYCERYL CAPRYLATE; POLYOXYL 40 HYDROGENATED CASTOR OIL; WATER

WELMATE Anti-Diarrheal (Loperamide HCl) Softgels

Active ingredient (in each softgel)

Loperamide HCl 2 mg

Purpose

Anti-diarrheal

Use

Controls symptoms of diarrhea, including Travelers’ Diarrhea

Warnings

Allergy alert: Do not use if you have ever had a rash or other allergic reaction to Loperamide HCl.

Heart alert: Taking more than directed can cause serious heart problems or death.

Do not use:

- if you have bloody or black stool
- in children under 12 years of age

Ask a doctor before use if you have:

- fever
- mucus in the stool
- a history of liver disease
- a history of abnormal heart rhythm
- Ask a doctor before use if you are taking a prescription drug. Loperamide may interact with certain prescription drugs.

When using this product

tiredness, drowsiness or dizziness may occur. Be careful when driving or operating machinery.

Stop use and ask a doctor if

- symptoms get worse
- diarrhea lasts more than 2 days
- you get abdominal swelling or bulging. These may be signs of a serious condition.

If pregnant or breast-feeding,

ask a health professional before use.

Keep out of reach of children.

In case of overdose, get medical help or contact a Poison Control Center (1-800-222-1222) right away.

Directions

- drink plenty of clear fluids to help prevent dehydration caused by diarrhea
- not for use in children under 12 years of age
- adults and children 12 years and over: 2 softgels after the first loose stool; 1 softgel after each subsequent loose stool; but no more than 4 softgels in 24 hours

Other information

- do not use if blister unit is torn or open
- store at 20°- 25°C (68° - 77°F)

Inactive ingredients

butylated hydroxyanisole, edible ink, FD&C Blue #1, gelatin, glycerin, glyceryl caprylate, polyoxyl 40 hydrogenated castor oil, purified water.

Questions?

call toll-free 1-800-935-6737